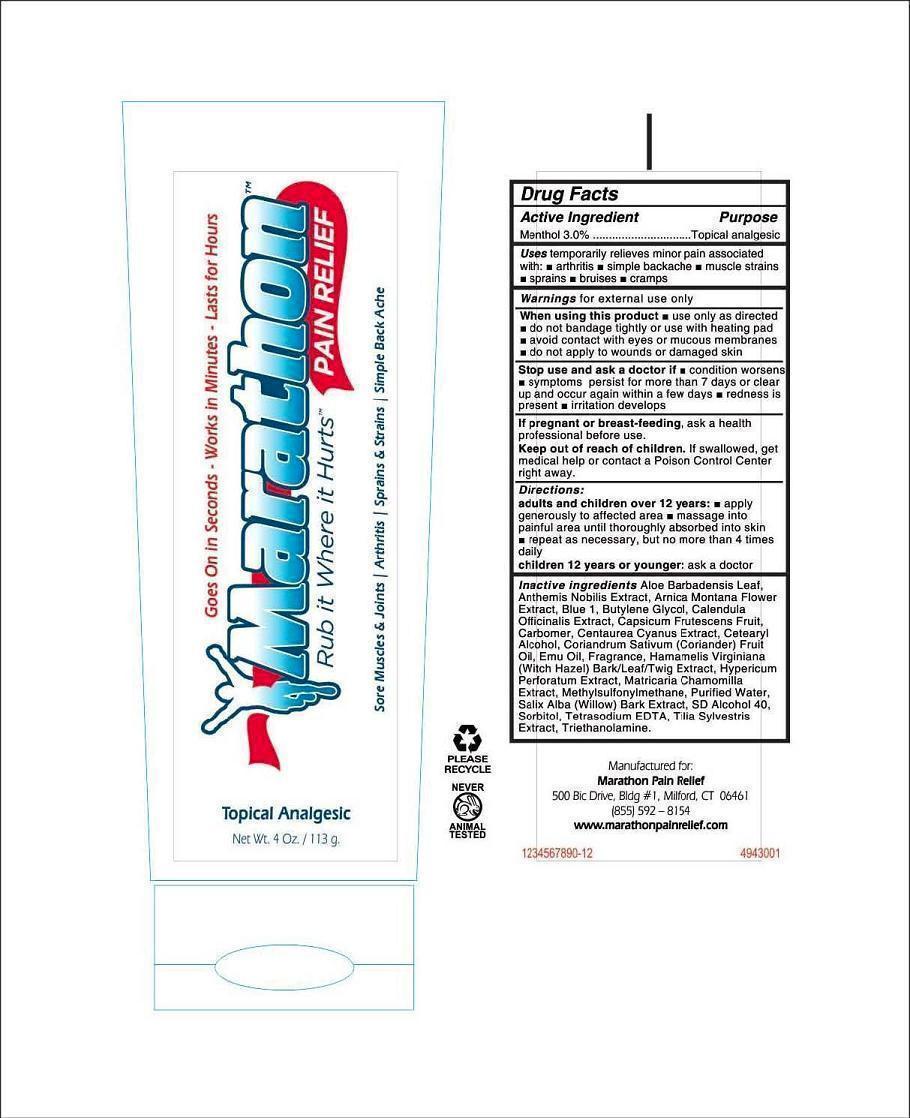 DRUG LABEL: Marathon Pain Relief
NDC: 58133-001 | Form: LOTION
Manufacturer: Cosmetic Specialty labs, Inc.
Category: otc | Type: HUMAN OTC DRUG LABEL
Date: 20130327

ACTIVE INGREDIENTS: menthol 3 g/100 g
INACTIVE INGREDIENTS: ALOE VERA LEAF; CHAMAEMELUM NOBILE FLOWER; ARNICA MONTANA FLOWER; FD&C BLUE NO. 1; BUTYLENE GLYCOL; CALENDULA OFFICINALIS FLOWER; CAPSICUM; CARBOMER 934; CENTAUREA CYANUS FLOWER; CETOSTEARYL ALCOHOL; CORIANDER OIL; EMU OIL; HAMAMELIS VIRGINIANA TOP; HYPERICUM PERFORATUM; CHAMOMILE; DIMETHYL SULFONE; WATER; SALIX ALBA BARK; ISOPROPYL ALCOHOL; SORBITOL; EDETATE SODIUM; TILIA X EUROPAEA FLOWER; TROLAMINE

ACTIVE INGREDIENT

Menthol 3.0%

PURPOSE

Topical analgesic

KEEP OUT OF REACH OF CHILDREN

If swallowed, get medical help or contact a poison control center right away.

USES

Temporarily relieves minor pain associated with

- arthritis
- simple backache
- muscle strains
- sprains
- bruises
- cramps

WARNINGS

for external use only

When using this product

- use only as directed
- do not bandage tightly or use with heating pad
- avoid contact with eyes or mucus membranes
- do not apply to wounds or damaged skin

Stop using and ask a doctor if

- condition worsens
- symptoms persist for more than 7 days or clear up and occur again within a few days
- redness is present
- irritation deveops

If pregnant or breast-feeding

ask a health professional before use

DIRECTIONS

adults and children over 12 years

- apply generously to affected area
- massage into painful area until throughly absorbed into skin
- repeat as necessary, but no more than 4 times daily

children 12 years or younger

ask a doctor

INACTIVE INGREDIENTS

Aloe Barbadensis Leaf, Anthemis Nobilis Extract, Arnica Montana Flower Extract, Blue 1, Butylene Glycol, Calendula Officinalis Extract, Capsicum rutescens Fruit, Carbomer, Centaurea Cyanus Extract, Cetearyl Alcohol, Coriandrum Sativum (Coriander) Fruit Oil, Emu Oil, Fragrance, Hamamelis Virginiana (Witch Hazel) Bark/Leaf/Twig Extract, Hypericum Perforatum Extract, Matricaria Chamomilla Extract, Methylsulfonylmethane, Purified Water, Salix Alba (Willow) Baril Extract, SD Alcohol 40, Sorbitol, Tetrasodium EDTA, Tilia Sylvestris Extract, Triethanolamine.